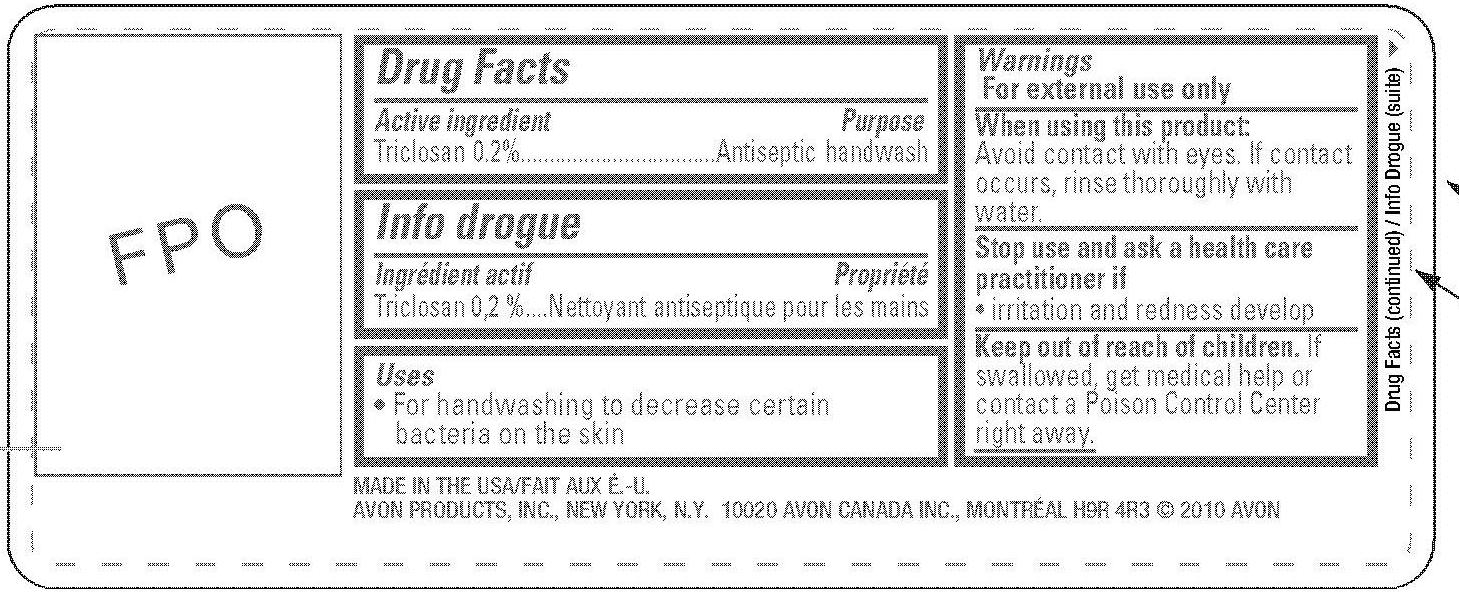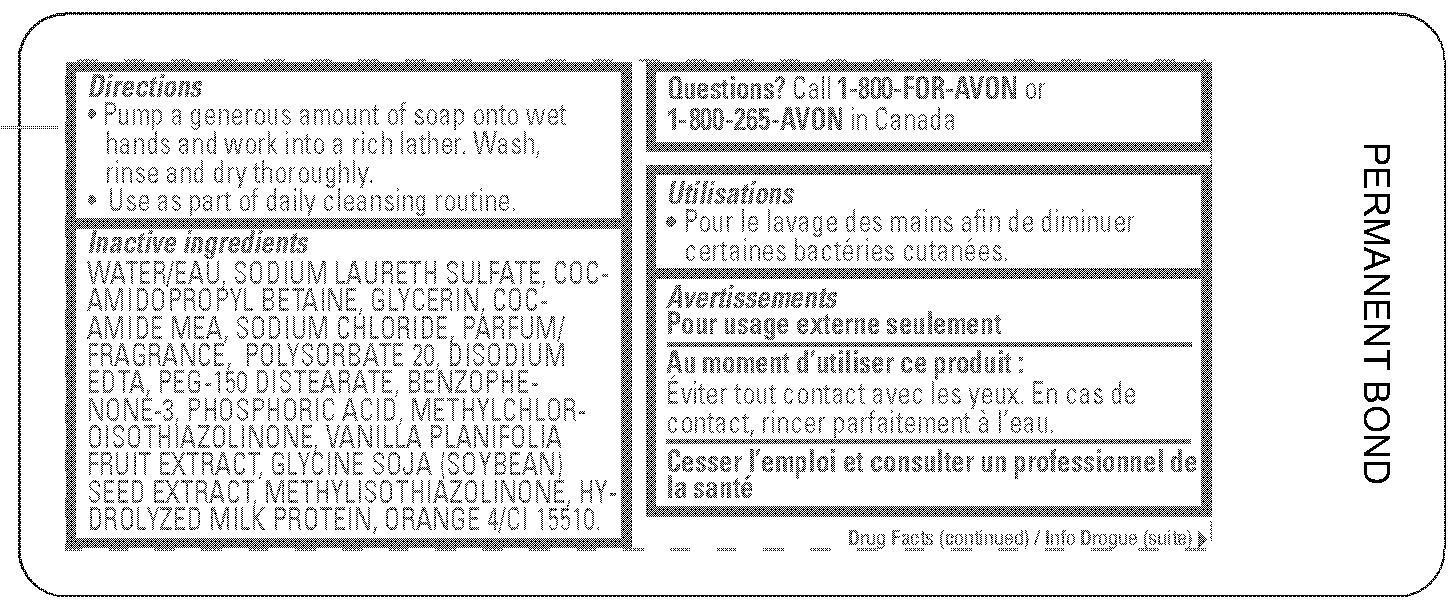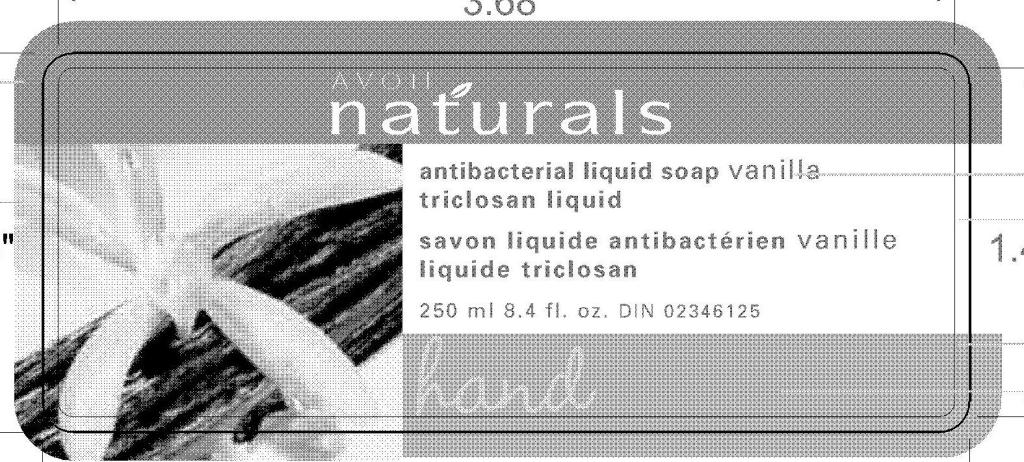 DRUG LABEL: Naturals
NDC: 10096-0212 | Form: LIQUID
Manufacturer: Avon Products, Inc.
Category: otc | Type: HUMAN OTC DRUG LABEL
Date: 20100609

ACTIVE INGREDIENTS: TRICLOSAN 0.5 mL/250 mL
INACTIVE INGREDIENTS: WATER; SODIUM LAURETH SULFATE; COCAMIDOPROPYL BETAINE; GLYCERIN; SODIUM CHLORIDE; POLYSORBATE 20; PEG-150 DISTEARATE; PHOSPHORIC ACID; METHYLCHLOROISOTHIAZOLINONE; METHYLISOTHIAZOLINONE

Drug Facts

Active ingredient Purpose

Triclosan 0.20%..................................Antiseptic handwash

Uses

- for handwashing to decrease certain bacteria on the skin

Warnings
For external use only

When using this product:
Avoid contact with eyes. If contact occurs, rinse thoroughly with water.

Stop use and ask a healthcare practitioner if

- irritation and redness develop

Keep out of reach of children. If swallowed, get medical help or contact a poison control center right away.

Directions

- Pump a generous amount of soap onto wet hands and work into a rich lather. Wash, rinse and dry thoroughly.
- Use as part of daily cleansing routine.

Inactive Ingredients

WATER/EAU
SODIUM LAURETH SULFATE
COCAMIDOPROPYL BETAINE
GLYCERIN
COCAMIDE MEA
SODIUM CHLORIDE
PARFUM/FRAGRANCE
POLYSORBATE 20
DISODIUM EDTA
PEG-150 DISTEARATE
BENZOPHENONE-3
PHOSPHORIC ACID
METHYLCHLOROISOTHIAZOLINONE
VANILLA PLANIFOLIA FRUIT EXTRACT
GLYCINE SOJA (SOYBEAN) SEED EXTRACT
METHYLISOTHIAZOLINONE
HYDROLYZED MILK PROTEIN
ORANGE 4/CI 15510

QUESTIONS

Questions? Call 1-800-FOR-AVON or 1-800-265-AVON in Canada